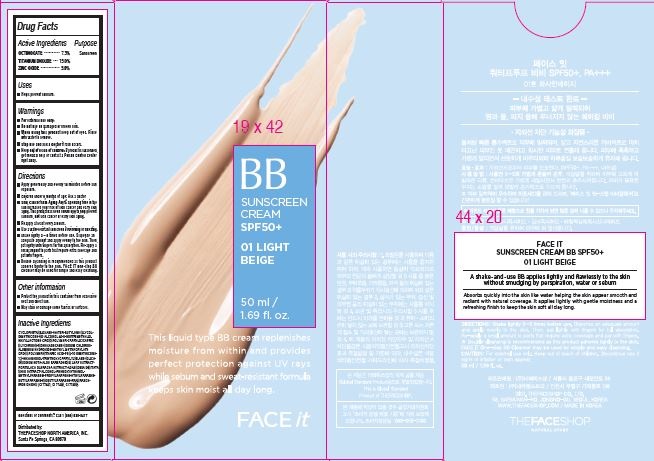 DRUG LABEL: FACE it
NDC: 51523-378 | Form: CREAM
Manufacturer: THEFACESHOP CO., LTD.
Category: otc | Type: HUMAN OTC DRUG LABEL
Date: 20141120

ACTIVE INGREDIENTS: Octinoxate 3.65 g/50 mL; Titanium Dioxide 7.5 g/50 mL; Zinc Oxide 2.95 g/50 mL
INACTIVE INGREDIENTS: WATER

Active Ingredients

OCTINOXATE • • • • • • • 7.3%

TITANIUM DIOXIDE • • • 15.0%

ZINC OXIDE • • • • • • • • 5.9%

Purpose

Sunscreen

Sunscreen

Sunscreen

Warnings

For external use only.

Do not use on damaged or broken skin.

When using this product keep out of eyes. Rinse

with water to remove.

Stop use and ask a doctor if rash occurs.

Keep out of reach of children. If product is swallowed,

get medical help or contact a Poison Control Center

right away.

Directions

Apply generously and evenly 15 minutes before sun

exposure.

Children under 6 months of age: Ask a doctor

Skin Cancer/Skin Aging Alert: Spending time in the

sun increases your risk of skin cancer and early skin

aging. This product has been shown only to help prevent

sunburn, not skin cancer or early skin aging.

Reapply at least every 2 hours.

Use a water-resistant sunscreen if swimming or sweating.

Shake lightly 3 – 5 times before use. Dispense an

adequate amount and apply evenly to the skin. Then,

pat lightly with fingers for full absorption. Re-apply a

small amount to parts that require extra coverage and

pat with fingers.

Double cleansing is recommended as this product

adheres tightly to the skin. FACE IT One-ste p BB

Cleanser may be used for simple and easy cleansing.

Other information

Protect the product in this container from excessive heat and direct sun.

May stain or damage some fabrics or surfaces.

Inactive Ingredients

CYCLOPENTASILOXANE•WATER•BUTYLENE GLYCOL•

DIMETHICONE•SD ALCOHOL 40-B•HDI/TRIMETHYLOL

HEXYLLACTONE CROSSPOLYMER•CAPRYLIC/CAPRIC

GLYCERIDES•ISOHEXADECANE•SODIUM CHLORIDE•

ALUMINUM HYDROXIDE•METHYL METHACRYLATE

CROSSPOLYMER•STEARIC ACID•PEG-10 DIMETHICONE•

1,2-HEXANEDIOL•TRIETHOXYCAPRYLYLSILANE•SILICA•

DISODIUM EDTA•ALOE BARBADENSIS LEAF EXTRACT•

PORTULACA OLERACEA EXTRACT•ADANSONIA DIGITATA

SEED EXTRACT•ALCOHOL•PHENOXYETHANOL•

METHYLPARABEN•PROPYLPARABEN•ETHYLPARABEN•

BUTYLPARABEN•ISOBUTYLPARABEN•FRAGRANCE•

IRON OXIDES (CI 77491, CI 77492, CI 77499)

Questions or comments? Call 1 (866) 638-8417

Distributed by:

THEFACESHOP NORTH AMERICA, INC.

Santa Fe Springs, CA 90670

PACKAGE LABEL

BB

SUNSCREEN

CREAM

SPF50+

01 LIGHT

BEIGE